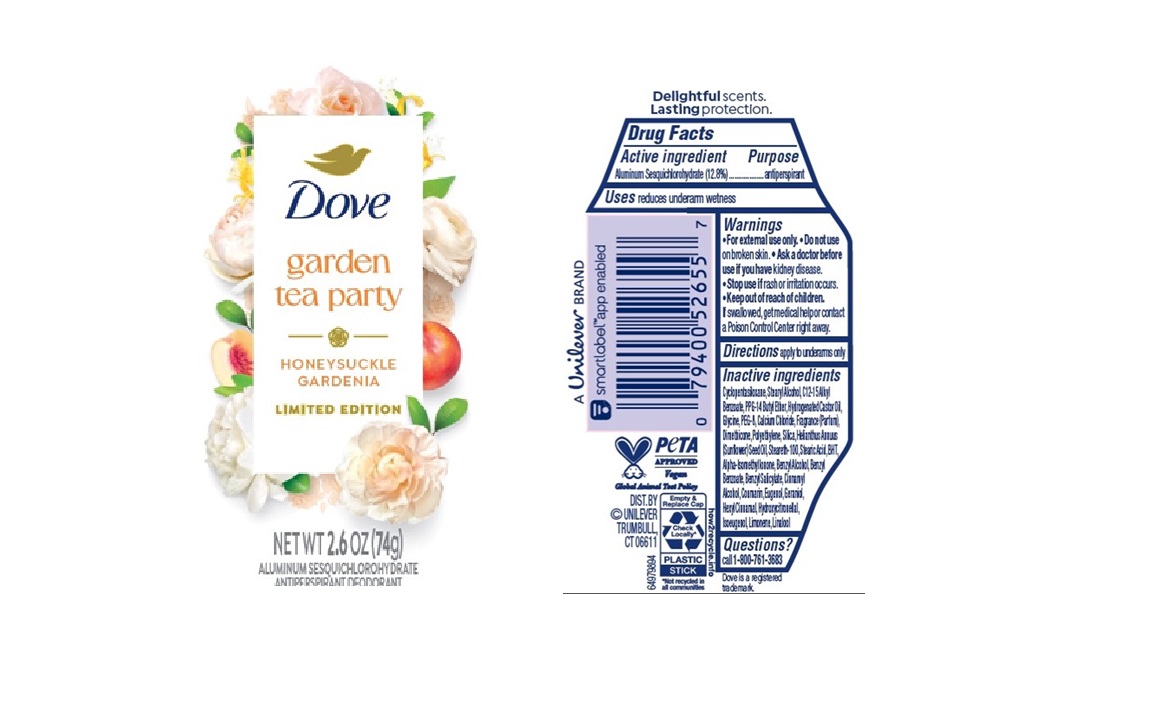 DRUG LABEL: Dove
NDC: 64942-2374 | Form: STICK
Manufacturer: Conopco d/b/a Unilever
Category: otc | Type: HUMAN OTC DRUG LABEL
Date: 20250501

ACTIVE INGREDIENTS: ALUMINUM SESQUICHLOROHYDRATE 12.8 g/100 g
INACTIVE INGREDIENTS: CINNAMYL ALCOHOL; ISOEUGENOL; HEXYL CINNAMAL; CALCIUM CHLORIDE; GERANIOL; GLYCINE; BENZYL ALCOHOL; BENZYL BENZOATE; BHT; HYDROGENATED CASTOR OIL; PEG-8; DIMETHICONE; POLYETHYLENE; EUGENOL; ALPHA-ISOMETHYL IONONE; SILICON DIOXIDE; STEARETH-100; CYCLOPENTASILOXANE; STEARYL ALCOHOL; C12-15 ALKYL BENZOATE; HELIANTHUS ANNUUS (SUNFLOWER) SEED OIL; STEARIC ACID; BENZYL SALICYLATE; LIMONENE, (+)-; LINALOOL; PPG-14 BUTYL ETHER; COUMARIN; HYDROXYCITRONELLAL

Dove Garden Tea Party Honeysuckle Gardenia Limited Edition Antiperspirant

DESCRIPTION

Dove Garden Tea Party Honeysuckle Gardenia Limited Edition Antiperspirant

ACTIVE INGREDIENT

ALUMINUM SESQUICHLOROHYDRATE (12.8%)

PURPOSE

antiperspirant

INDICATIONS AND USAGE

reduces underarm wetness

WARNINGS

For external use only.
Do not use on broken skin.
Ask a doctor before use if you have kidney disease.
Stop use if rash or irritation occurs.

Keep out of reach of children. If swallowed, get medical help or contact a Poison Control Center right away

DOSAGE AND ADMINISTRATION

apply to underarms only

INACTIVE INGREDIENT

cyclopentasiloxane, Stearyl Alcohol, C12-15 Alkyl Benzoate, PPG-14 Butyl Ether, Hydrogenated Castor Oil, Glycine, PEG-8, Calcium Chloride, Fragrance (Parfum) , Dimethicone, Polyethylene, Silica, Helianthus Annuus (Sunflower) Seed Oil,Steareth-100, StearicAcid,BHT, Alpha-Isomethyl Ionone, Benzyl Alcohol, Benzyl Benzoate, Benzyl Salicylate, Cinnamyl Alcohol, Coumarin, Eugenol, Geraniol, Hexyl Cinnamal, Hydroxycitronellal, Isoeugenol, Limonene, Linalool

QUESTIONS

Call 1-800-761-3683